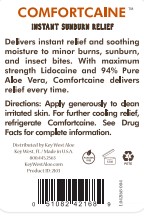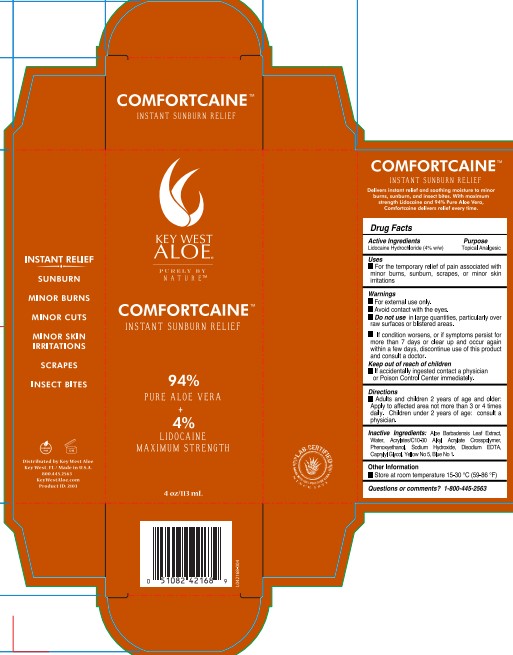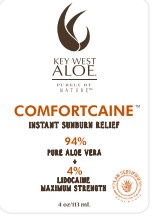 DRUG LABEL: Comfortcaine
NDC: 65008-005 | Form: GEL
Manufacturer: QS Key West Aloe, LLC
Category: otc | Type: HUMAN OTC DRUG LABEL
Date: 20251111

ACTIVE INGREDIENTS: LIDOCAINE HYDROCHLORIDE 40 mg/1 g
INACTIVE INGREDIENTS: ALOE VERA LEAF; WATER; CARBOMER INTERPOLYMER TYPE B (ALLYL PENTAERYTHRITOL CROSSLINKED); EDETATE DISODIUM; SODIUM HYDROXIDE; CAPRYLYL GLYCOL; PHENOXYETHANOL; FD&C YELLOW NO. 5; FD&C BLUE NO. 1

Comfortcaine

Active Ingredients

Lidocaine Hydrochloride (4% w/w)

Purpose

Topical Analgesic

Uses

• For the temporary relief of pain associated with minor burns, sunburn, scrapes, or minor skin irritations.

Warnings

• For external use only.

• Avoid contact with the eyes.

• Do not use in large quantities, particularly over raw surfaces or blistered areas.

• If condition worsens, or if symptoms persist for more than 7 days or clear up and occur again within a few days, discontinue use of this product and consult a doctor.

Keep out of reach of children

• If accidentally ingested contact a physician or Poison Control Center immediately.

Directions

• Adults and children 2 years of age or older: Apply to affected area not more than 3 or 4 times daily. Children under 2 years of age: consult a physician.

Inactive Ingredients:

Aloe Barbadensis Leaf Extract, Water, Acrylates/c10-30 Alkyl Acrylate Crosspolymer, Phenoxyethanol, Sodium Hydroxide, Disodium EDTA, Caprylyl Glycol, Yellow No 5, FD&C Blue No 1.

Other Information

• Store at room temperature 15-30°C (59-86°F)

Questions or comments?

1-800-445-2563